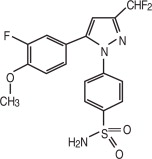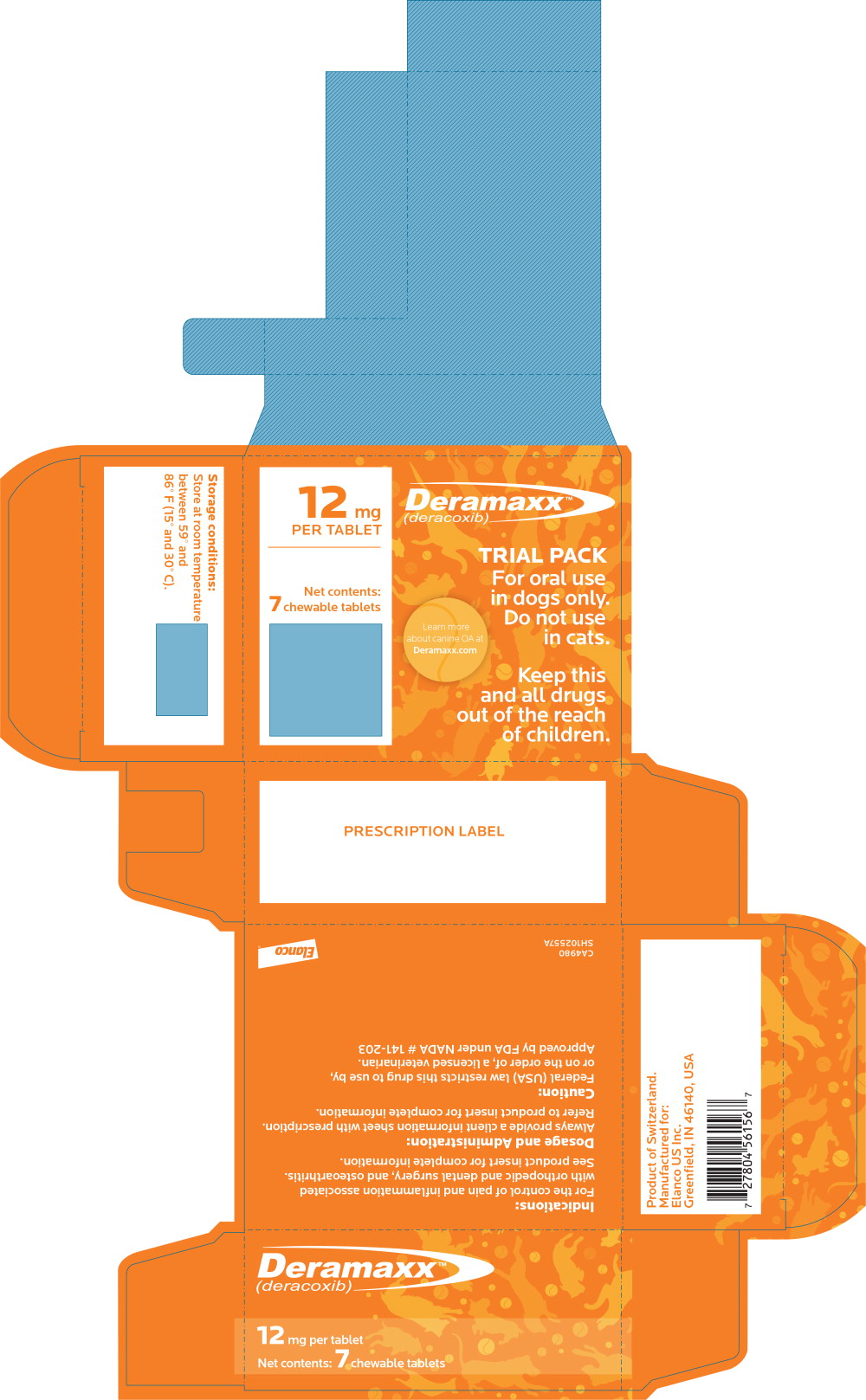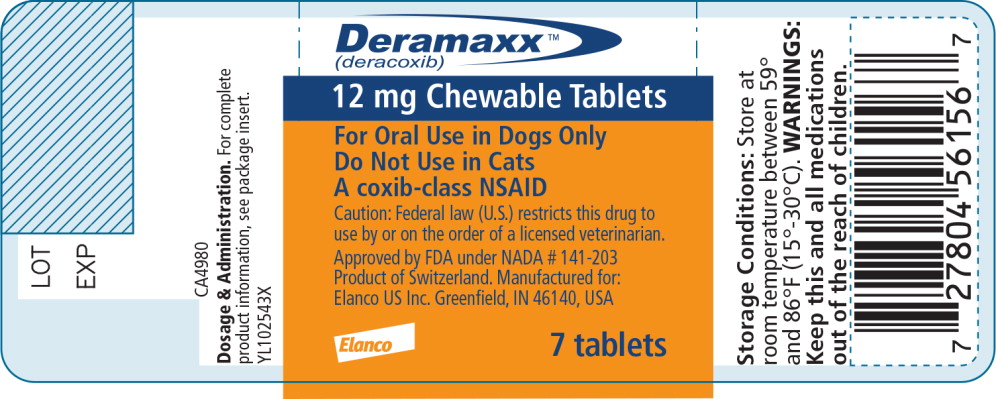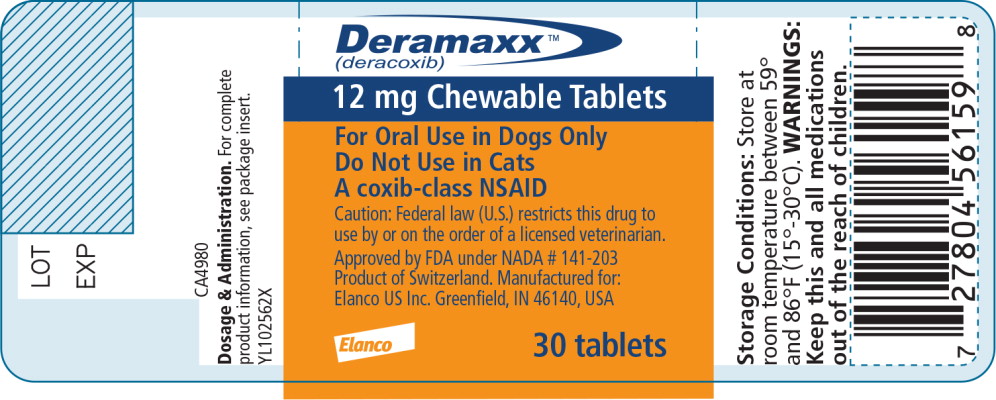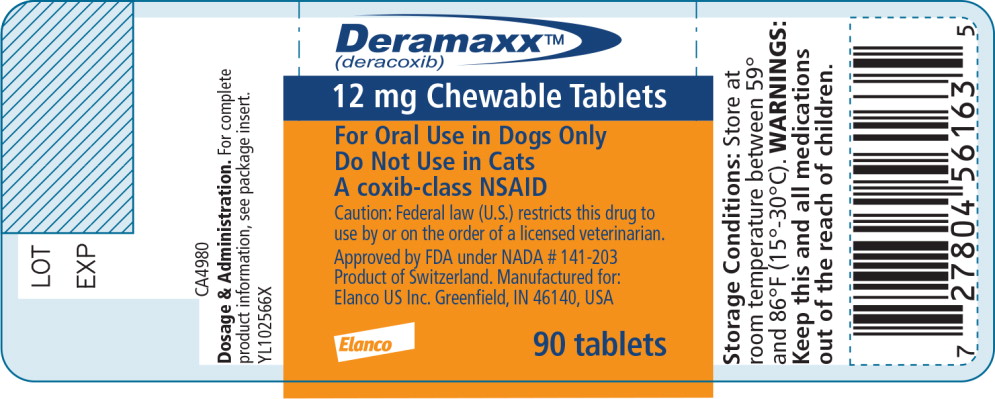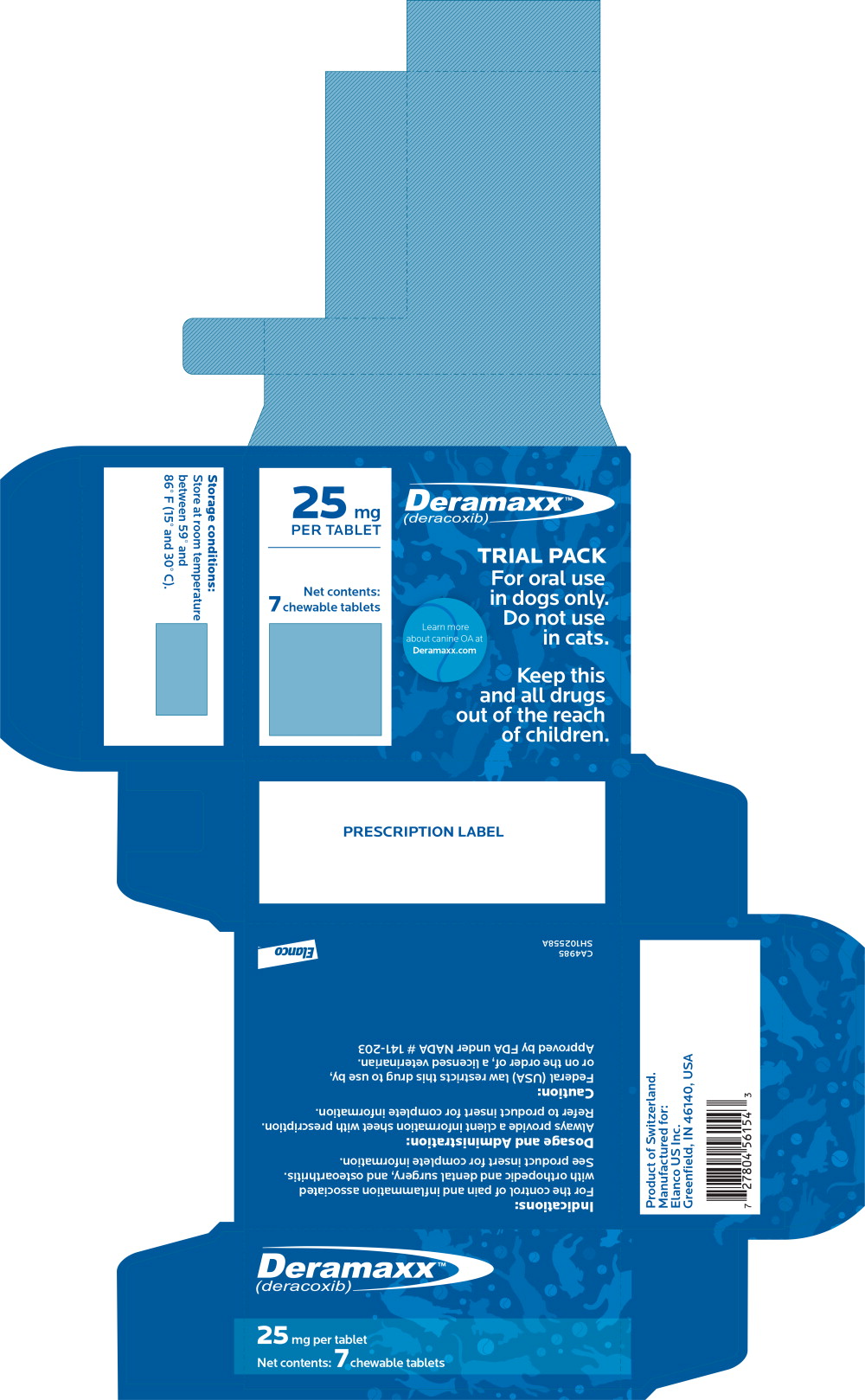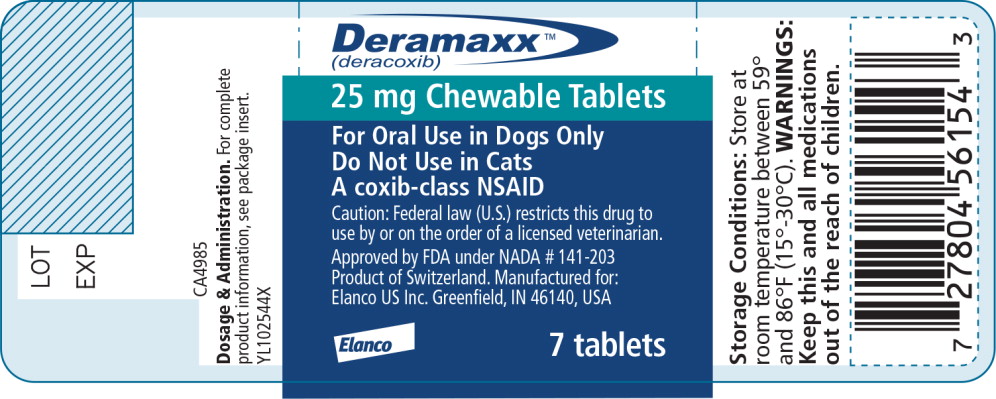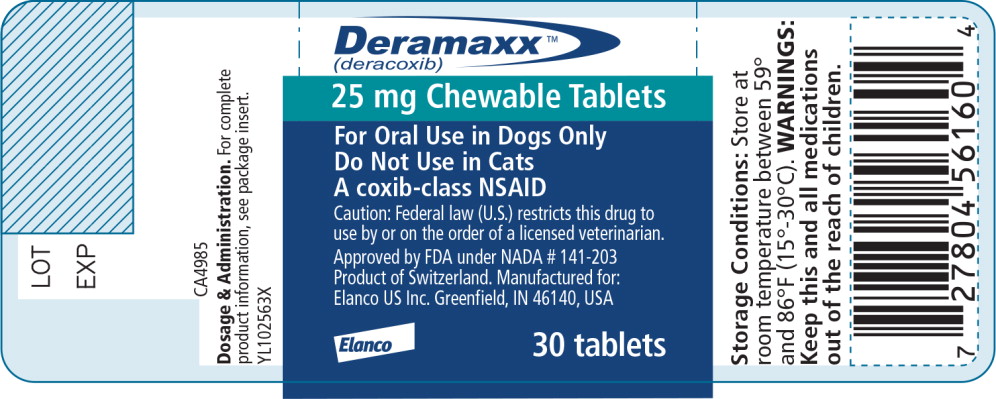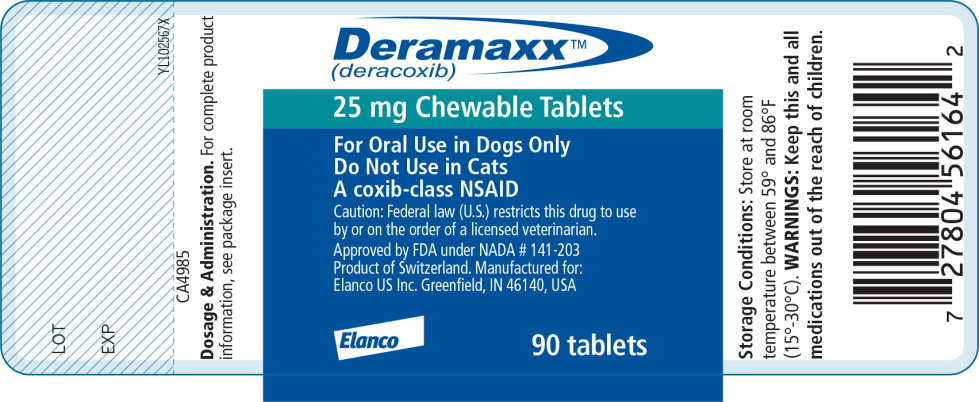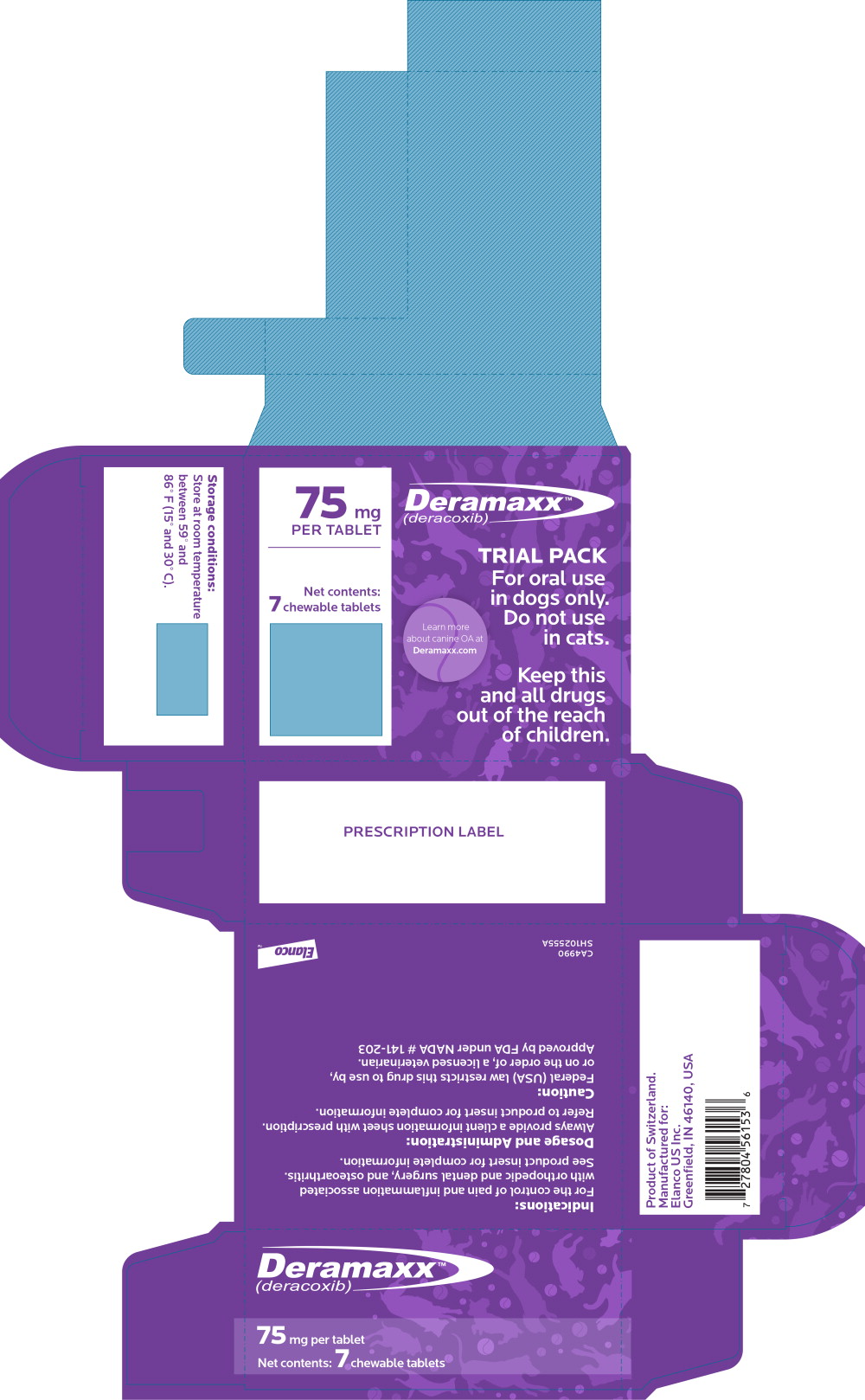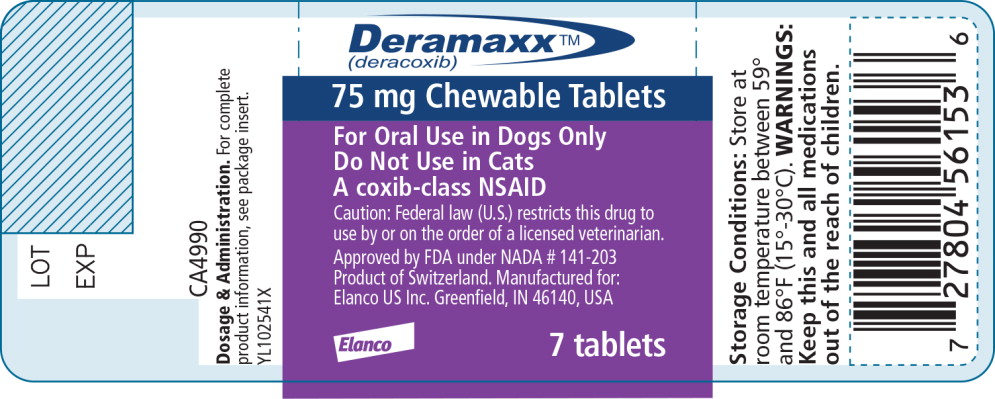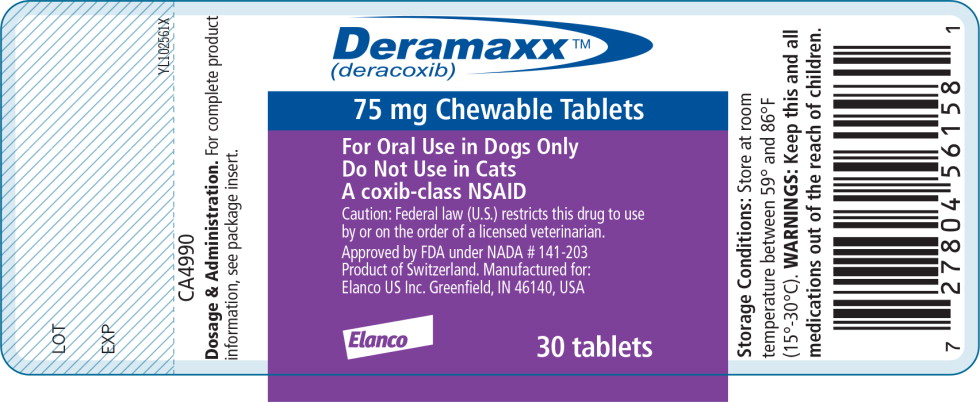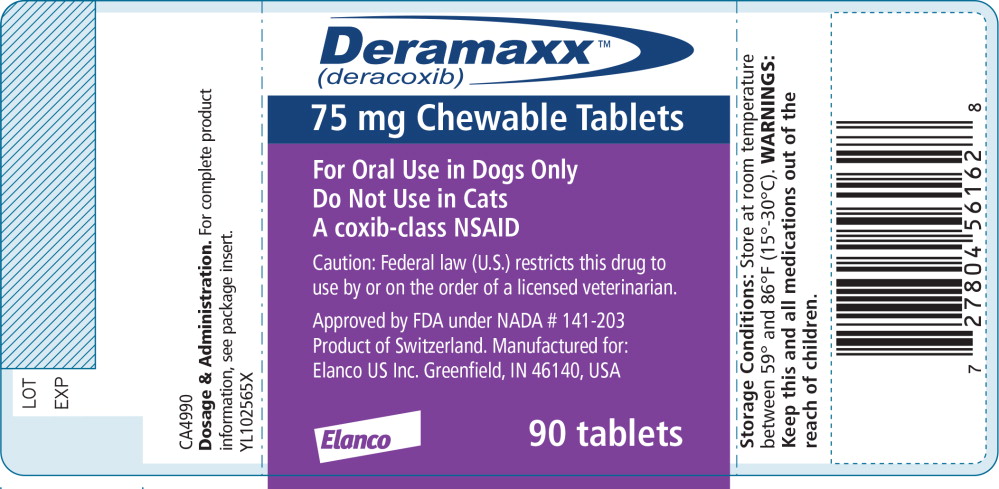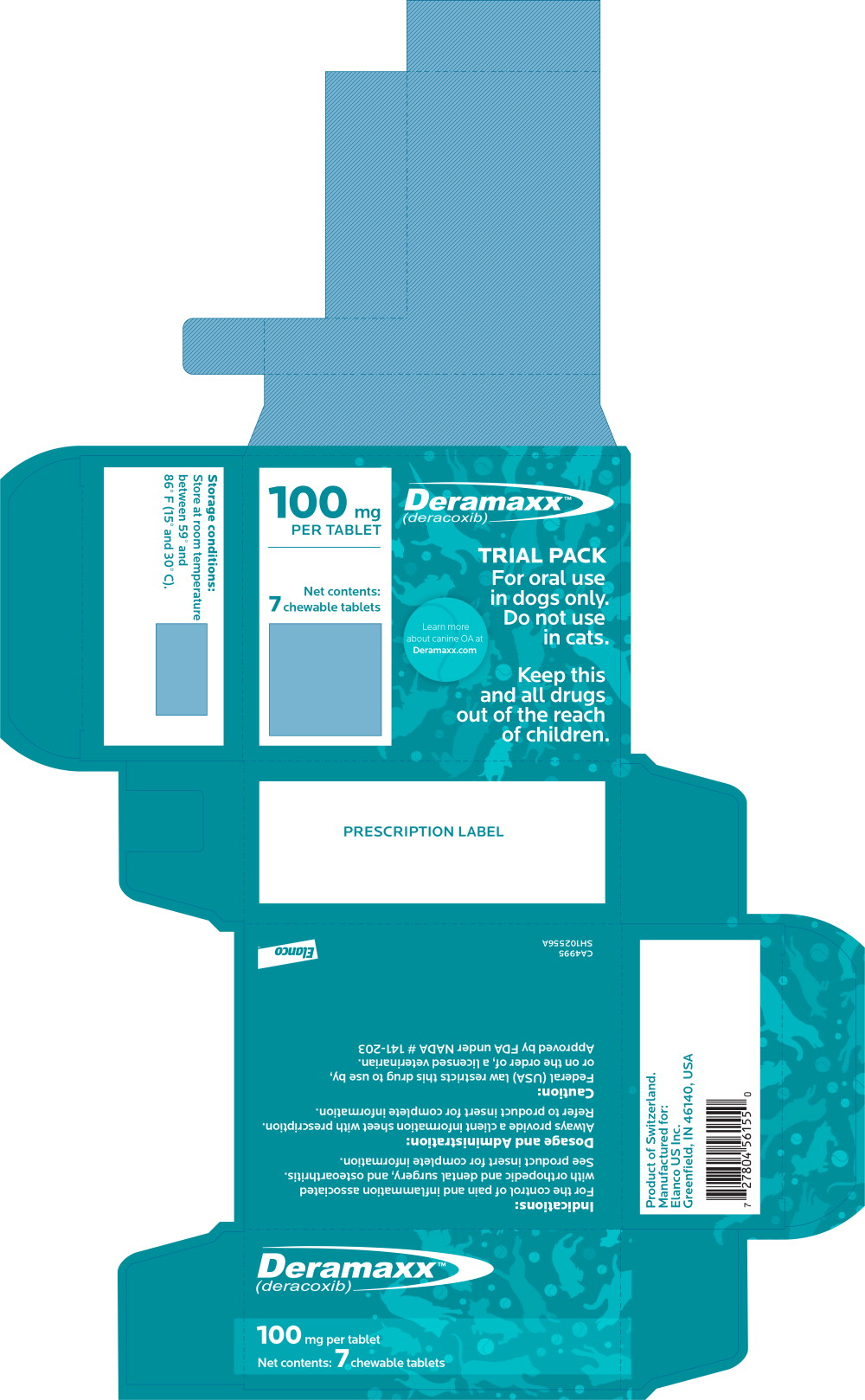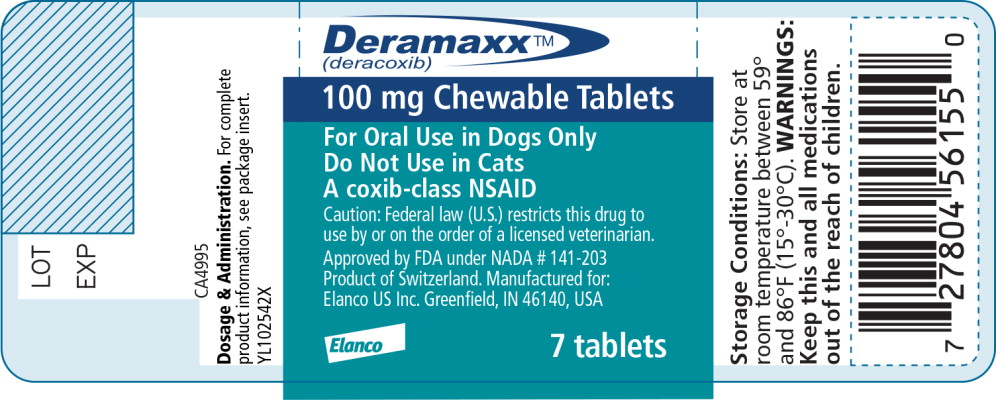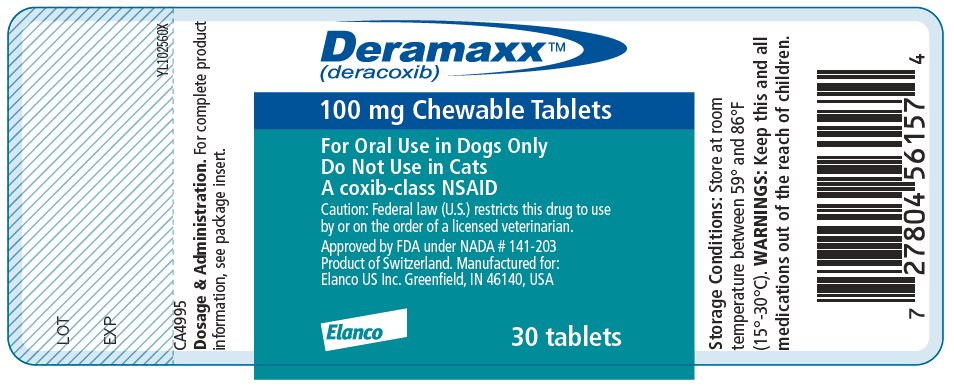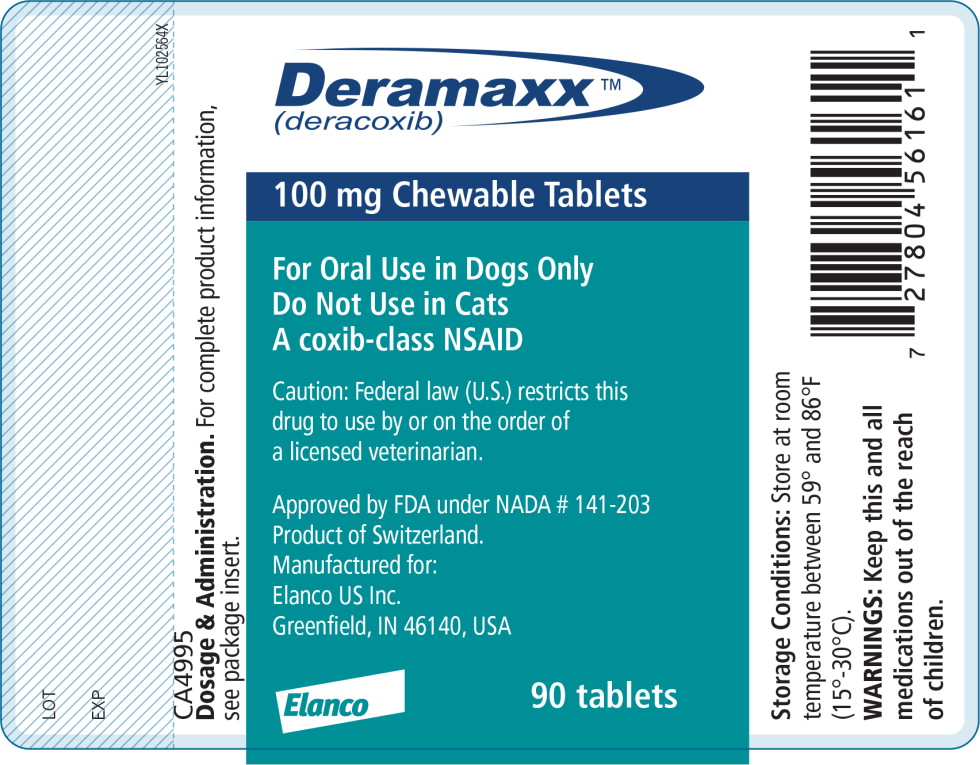 DRUG LABEL: Deramaxx
NDC: 58198-5218 | Form: TABLET, CHEWABLE
Manufacturer: Elanco US Inc.
Category: animal | Type: PRESCRIPTION ANIMAL DRUG LABEL
Date: 20260107

ACTIVE INGREDIENTS: deracoxib 12 mg/1 1

Deramaxx™
(deracoxib)

Chewable Tablets

For Oral Use in Dogs Only

Do Not Use in Cats

Caution:

Federal Law (U.S.) restricts this drug to use by or on the order of a licensed veterinarian.

Description:

DERAMAXX (deracoxib) is a non-narcotic, non-steroidal anti-inflammatory drug (NSAID) of the coxib class. DERAMAXX tablets are round, biconvex, chewable tablets that contain deracoxib formulated with beefy flavoring. The molecular weight of deracoxib is 397.38. The empirical formula is C17-H14-F3-N3O3-S. Deracoxib is 4-[3-(difluoromethyl)-5-(3-fluoro-4-methoxyphenyl)-1H-pyrazole-1-yl] benzenesulfonamide, and can be termed a diaryl substituted pyrazole. The structural formula is:

Clinical Pharmacology

Mode of Action:

DERAMAXX tablets are a member of the coxib class of non-narcotic, non-steroidal, cyclooxygenase-inhibiting anti-inflammatory drugs for the control of postoperative pain and inflammation associated with orthopedic and dental surgery and for the control of pain and inflammation associated with osteoarthritis in dogs.

Data indicate that deracoxib inhibits the production of PGE1 and 6-keto PGF1 by its inhibitory effects on prostaglandin biosynthesis.^1 Deracoxib inhibited COX-2 mediated PGE2 production in LPS-stimulated human whole blood.^2

Cyclooxygenase-1 (COX-1) is the enzyme responsible for facilitating constitutive physiological processes (e.g., platelet aggregation, gastric mucosal protection, renal perfusion).^3 Cyclooxygenase-2 (COX-2) is responsible for the synthesis of inflammatory mediators.^4 Both COX isoforms are constitutively expressed in the canine kidney.^5 At doses of 2-4 mg/kg/day, DERAMAXX tablets do not inhibit COX-1 based on in vitro studies using cloned canine cyclooxygenase.^6 The clinical relevance of this in vitro data has not been shown.

Although the plasma terminal elimination half-life for DERAMAXX tablets is approximately 3 hours, a longer duration of clinical effectiveness is observed.

Summary pharmacokinetics of DERAMAXX tablets are listed in Table 1.

Table 1: Pharmacokinetics of Deracoxib
Parameter | Value
Tmaxa | 2 hours
Oral Bioavailability (F)a | > 90% at 2 mg/kg
Terminal elimination half-lifeb | 3 hours at 2-3 mg/kg 19 hours at 20 mg/kg
Systemic Clearanceb | ~ 5 ml/kg/min at 2 mg/kg ~1.7 ml/kg/min at 20 mg/kg
Volume of Distributionc | ~ 1.5 L/kg
Protein bindingd | > 90%
aValues obtained following a single 2.35 mg/kg dose
bEstimates following IV administration of deracoxib as an aqueous solution
cBased upon a dose of 2 mg/kg of deracoxib
dBased upon in vitro plasma concentrations of 0.1, 0.3, 1.0, 3.0, 10.0 μg/ml

Non-linear elimination kinetics are exhibited at doses above 8 mg/kg/day, at which competitive inhibition of constitutive COX-1 may occur.

Deracoxib is not excreted as parent drug in the urine. The major route of elimination of deracoxib is by hepatic biotransformation producing four major metabolites, two of which are characterized as products of oxidation and o-demethylation. The majority of deracoxib is excreted in feces as parent drug or metabolite.

Large intersubject variability was observed in drug metabolite profiles of urine and feces. No statistically significant differences between genders were observed.

Indications and Usage:

Always provide “Information for Dog Owners” Sheet with prescription. Carefully consider the potential benefits and risk of DERAMAXX and other treatment options before deciding to use DERAMAXX. Use the lowest effective dose for the shortest duration consistent with individual response.

Osteoarthritis Pain and Inflammation:

DERAMAXX Chewable Tablets are indicated for the control of pain and inflammation associated with osteoarthritis in dogs.

Dosage and Administration:

Osteoarthritis Pain and Inflammation: 0.45 – 0.91 mg/lb/day (1 to 2 mg/kg/ day) as a single daily dose, as needed.

Dogs needing a dose of less than 12.5 mg can only be accurately dosed through use of the 12 mg tablet, which can be broken in half to provide 6 mg. Do not attempt to accurately dose smaller dogs through the use of breaking larger tablets. Inaccurate dosing may result in adverse drug events (see Adverse Reactions, Animal Safety, and Post-Approval Experience).

Postoperative Orthopedic Pain and Inflammation:

DERAMAXX Chewable Tablets are indicated for the control of postoperative pain and inflammation associated with orthopedic surgery in dogs.

Dosage and Administration:

Postoperative Orthopedic Pain and Inflammation: 1.4 – 1.8 mg/lb/day (3 to 4 mg/kg/day) as a single daily dose, as needed, not to exceed 7 days of administration.

Dogs needing a dose of less than 12.5 mg can only be accurately dosed through use of the 12 mg tablet, which can be broken in half to provide 6 mg. Do not attempt to accurately dose smaller dogs through the use of breaking larger tablets. Inaccurate dosing may result in adverse drug events (see Adverse Reactions, Animal Safety and Post-Approval Experience).

Postoperative Dental Pain and Inflammation:

DERAMAXX Chewable Tablets are indicated for the control of postoperative pain and inflammation associated with dental surgery in dogs.

Dosage and Administration:

Postoperative Dental Pain and Inflammation: 0.45 – 0.91 mg/lb/day (1 to 2 mg/kg/day) as a single daily dose, for 3 days. The first dose should be given approximately 1 hour prior to dental surgery and subsequent doses should be given daily for up to two additional treatments.

Dogs needing a dose of less than 12.5 mg can only be accurately dosed through use of the 12 mg tablet, which can be broken in half to provide 6 mg. Do not attempt to accurately dose smaller dogs through the use of breaking larger tablets. Inaccurate dosing may result in adverse drug events (see Adverse Reactions, Animal Safety, and Post-Approval Experience).

Since DERAMAXX tablet bioavailability is greatest when taken with food, postprandial administration is preferable. However, DERAMAXX tablets have been shown to be effective under both fed and fasted conditions; therefore, they may be administered in the fasted state if necessary. For postoperative orthopedic and dental pain, administer DERAMAXX tablets prior to the procedure. Tablets are scored and dosage should be calculated in half-tablet increments. In clinical practice it is recommended to adjust the individual patient dose while continuing to monitor the dog's status until a minimum effective dose has been reached.

Contraindications:

Dogs with known hypersensitivity to deracoxib should not receive DERAMAXX.

Warnings:

Not for use in humans. Keep this and all medications out of reach of children. Consult a physician in case of accidental ingestion by humans. For use in dogs only. Do not use in cats.

Dogs needing a dose of less than 12.5 mg can only be accurately dosed through use of the 12 mg tablet, which can be broken in half to provide 6 mg. Do not attempt to accurately dose smaller dogs through the use of breaking larger tablets. Inaccurate dosing may result in adverse drug events (see Adverse Reactions, Animal Safety, and Post-Approval Experience).

All dogs should undergo a thorough history and physical examination before the initiation of NSAID therapy. Appropriate laboratory tests to establish hematological and serum biochemical baseline data prior to, and periodically during, administration of any NSAID is recommended. Owners should be advised to observe for signs of potential drug toxicity (see Adverse Reactions, Animal Safety and Post-Approval Experience) and be given an “Information for Dog Owners” Sheet.

Precautions:

Dogs needing a dose of less than 12.5 mg can only be accurately dosed through use of the 12 mg tablet, which can be broken in half to provide 6 mg. Do not attempt to accurately dose smaller dogs through the use of breaking larger tablets. Inaccurate dosing may result in adverse drug events (see Adverse Reactions, Animal Safety, and Post-Approval Experience).

Since NSAIDs possess the potential to produce gastrointestinal ulceration and/or perforation, concomitant use of DERAMAXX tablets with other anti-inflammatory drugs, such as NSAIDs or corticosteroids, should be avoided. As a class, NSAIDs may be associated with gastrointestinal, renal and hepatic toxicity. The following collective group of clinical signs has been reported with some serious gastrointestinal events, in decreasing order of reported frequency: anorexia, tachycardia, tachypnea, pyrexia, ascites, pale mucous membranes, dyspnea. In some cases, circulatory shock, collapse and cardiac arrest have also been reported. Sensitivity to drug-associated adverse events varies with the individual patient. Dogs that have experienced adverse reactions from one NSAID may experience adverse reactions from another NSAID. Patients at greatest risk for adverse events are those that are dehydrated, on concomitant diuretic therapy, or those with existing renal, cardiovascular, and/ or hepatic dysfunction. Plasma levels of deracoxib may increase in a greater than dose-proportional fashion above 8 mg/kg/day. DERAMAXX tablets have been safely used during field studies in conjunction with other common medications, including heartworm preventatives, anthelmintics, anesthetics, pre-anesthetic medications, and antibiotics. If additional pain medication is needed after a daily dose of DERAMAXX tablets, a non-NSAID/non-corticosteroid class of analgesic may be necessary. It is not known whether dogs with a history of hypersensitivity to sulfonamide drugs will exhibit hypersensitivity to DERAMAXX tablets. The safe use of DERAMAXX tablets in dogs younger than 4 months of age, dogs used for breeding, or in pregnant or lactating dogs has not been evaluated.

NSAIDs may inhibit the prostaglandins which maintain normal homeostatic function. Such anti-prostaglandin effects may result in clinically significant disease in patients with underlying or pre-existing disease that has not been previously diagnosed. Appropriate monitoring procedures should be employed during all surgical procedures. The use of parenteral fluids during surgery should be considered to decrease potential renal complications when using NSAIDs perioperatively. Concurrent administration of potentially nephrotoxic drugs should be carefully approached.

The use of concomitantly protein-bound drugs with DERAMAXX tablets has not been studied in dogs. Commonly used protein-bound drugs include cardiac, anticonvulsant and behavioral medications. The influence of concomitant drugs that may inhibit metabolism of DERAMAXX tablets has not been evaluated. Drug compatibility should be monitored in patients requiring adjunctive therapy. Consider appropriate washout times when switching from one NSAID to another or when switching from corticosteroid use to NSAID use.

Animal Safety:

In a 6-month study, dogs were dosed with DERAMAXX at 0, 2, 4, 6, 8 and 10 mg/kg with food once daily for 6 consecutive months. There were no abnormal feces, and no abnormal findings on clinical observations, food and water consumption, body weights, physical examinations, ophthalmoscopic evaluations, macroscopic pathological examinations, hematology, or buccal bleeding time. Urinalysis results showed hyposthenuria (specific gravity <1.005) and polyuria in one male and one female in the 6 mg/kg group after 6 months of treatment. After 6 months of treatment, the mean BUN values for dogs treated with 6, 8, or 10 mg/kg/day were 30.0, 35.3, and 48.2 mg/dL respectively. No effects were seen on any other clinical chemistry parameters, including other variables associated with renal physiology (serum creatinine, serum electrolytes, and urine sediment evaluation). Dose dependent focal renal tubular degeneration/regeneration was seen in some dogs treated at 6, 8, and 10 mg/kg/day. Focal renal papillary necrosis was seen in 3 dogs dosed at 10 mg/kg/day and in one dog dosed at 8 mg/kg/day. No renal lesions were seen at the label doses of 2 and 4 mg/kg/day. There was no evidence of gastrointestinal, hepatic, or hematopoietic pathology at any of the doses tested.

In a laboratory study, healthy young dogs were dosed with deracoxib tablets once daily, within 30 minutes of feeding, at doses of 0, 4, 6, 8, and 10 mg/kg body weight for 21 consecutive days. No adverse drug events were reported. There were no abnormal findings reported for clinical observations, food and water consumption, body weights, physical examinations, ophthalmic evaluations, organ weights, macroscopic pathologic evaluation, hematology, urinalyses, or buccal mucosal bleeding time. In the clinical chemistry results there was a statistically significant (p<0.0009) dose-dependent trend toward increased levels of blood urea nitrogen (BUN). Mean BUN values remained within historical normal limits at the label dose. No effects on other clinical chemistry values associated with renal function were reported. There was no evidence of renal, gastrointestinal, hepatic or biliary lesions noted during gross necropsy. Renal histopathology revealed trace amounts of tubular degeneration/regeneration in all dose groups including placebo, but no clear dose relationship could be determined. There was no histopathologic evidence of gastrointestinal, hepatic or biliary lesions.

In another study, micronized deracoxib in gelatin capsules was administered once daily to healthy young dogs at doses of 10, 25, 50, and 100 mg/kg body weight for periods up to 14 consecutive days. Food was withheld prior to dosing. Non-linear elimination kinetics occurred at all doses. At doses of 25, 50, and 100 mg/kg, reduced body weight, vomiting, and melena occurred. Necropsy revealed gross gastrointestinal lesions in dogs from all dose groups. The frequency and severity of the lesions increased with escalating doses. At 10 mg/kg, moderate diffuse congestion of gut associated lymphoid tissues (GALT) and erosions/ulcers in the jejunum occurred. At 100 mg/kg, all dogs exhibited gastric ulcers and erosions/ulcerations of the small intestines. There were no hepatic or renal lesions reported at any dose in this study.

In a 13-week study, deracoxib in gelatin capsules was administered to healthy dogs at doses of 0, 2, 4, and 8 mg/kg/day. No test-article related changes were identified in clinical observations, physical exams, or any of the other parameters measured. One dog in the 8 mg/kg dose group died from bacterial septicemia secondary to a renal abscess. The relationship between deracoxib administration and the renal abscess is not clear.

Palatability:

DERAMAXX tablets were evaluated for palatability in 100 client-owned dogs of a variety of breeds and sizes. Dogs received two doses of DERAMAXX tablets, one on each of two consecutive days. DERAMAXX tablets were accepted by 94% of dogs on the first day of dosing and by 92% of dogs on the second day of dosing.

Effectiveness:

DERAMAXX tablets were evaluated in masked, placebo-controlled multi-site field studies involving client-owned animals to determine effectiveness.

Osteoarthritis Pain and Inflammation Field Study:

Two hundred and nine (209) client-owned dogs with clinical and radiographic signs of osteoarthritis of at least one appendicular joint were enrolled in this study. A total of 194 dogs were included in the safety evaluation and a total of 181 dogs were included in the effectiveness evaluation. The effectiveness of DERAMAXX tablets in the control of pain and inflammation associated with osteoarthritis was demonstrated in a placebo-controlled, masked study evaluating the anti-inflammatory and analgesic effects of DERAMAXX tablets. Tablets were administered by the owner at approximately 1-2 mg/kg/day for forty-three (43) consecutive days.

In general, statistically significant (p≤ 0.05) differences in favor of DERAMAXX were seen for force plate parameters (vertical impulse area, peak vertical force) and owner evaluations (quality of life, lameness and overall level of activity).

The results of this field study demonstrate that DERAMAXX tablets, when administered at 1-2 mg/kg/day for 43 days, are effective for the control of pain and inflammation associated with osteoarthritis.

Adverse Reactions:

DERAMAXX (deracoxib) was well tolerated and the incidence of clinical adverse reactions was comparable in DERAMAXX and placebo-treated animals. A total of 209 dogs of 41 breeds, 1-14 years old, weighing 17-177 lbs were included in the field safety analysis. The following table shows the number of dogs displaying each adverse reaction.

Abnormal Health Findings in the Osteoarthritis Field Study^1
Clinical Observation | DERAMAXX (deracoxib) tablets N = 105 | Placebo N = 104
Vomiting | 3 | 4
Diarrhea/soft stool | 3 | 2
Weight loss | 1 | 0
Abdominal pain (splinting) | 0 | 1
Seizure | 1 | 0
Lethargy | 0 | 1
Pyoderma/Dermatitis | 2 | 0
Unilateral conjunctivitis | 1 | 0
Scleral injection | 0 | 1
Hematuria/UTI | 1 | 0
Splenomegaly* | 1 | 0
Grade II murmur systolic | 1 | 0
^1Dogs may have experienced more than one adverse reaction during the study.
* This dog was less active and eating less on enrollment, with elevated WBC, amylase, and AST and died 1 month after exiting the study. The dog was withdrawn from the study on Day 17 with anorexia, lethargy and a suspicion of diarrhea. Follow-up laboratory analyses revealed hypoalbuminemia, hyperphosphatemia, elevated AST and decreased BUN. Follow-up treatment included other anti-inflammatories and antibiotics.

Complete blood count, serum chemistry, and buccal bleeding time analysis were conducted at the beginning and end of the trial. Mean values of all CBC and chemistry results for both DERAMAXX and placebo-treated dogs were within normal limits. There was no statistically significant difference in the buccal bleeding time between DERAMAXX and placebo-treated dogs before or after the study, and all results remained within normal limits (less than 5 minutes). The results of this field study demonstrate that DERAMAXX is safe and effective for the control of pain and inflammation associated with osteoarthritis in dogs.

During this trial, dogs were safely treated with a variety of commonly used medications, including antibiotics, anti-parasiticides, topical flea adulticides and thyroid supplements.

The results of this field study demonstrate that DERAMAXX tablets are well tolerated when administered at 1-2 mg/kg/day for up to 43 days for the control of pain and inflammation associated with osteoarthritis.

Postoperative Orthopedic Pain and Inflammation Field Study:

In this study, 207 dogs admitted to veterinary hospitals for repair of a cranial cruciate injury were randomly administered DERAMAXX tablets or a placebo. Drug administration started the evening before surgery and continued once daily for 6 days postoperatively. Effectiveness was evaluated in 119 dogs and safety was evaluated in 207 dogs. Statistically significant differences in favor of DERAMAXX tablets were found for lameness at walk and trot, and pain on palpation values at all post-surgical time points. The results of this field study demonstrate that DERAMAXX tablets, when administered daily for 7 days are effective for the control of postoperative pain and inflammation associated with orthopedic surgery.

Adverse Reactions:

A total of 207 dogs of forty-three (43) different breeds, 1-15 years old, weighing 7-141 lbs were included in the field safety analysis. The following table shows the number of dogs displaying each adverse reaction.

Abnormal Health Findings inThe Postoperative Orthopedic Pain Field Study^1
Clinical Observation | DERAMAXX (deracoxib) tablets N = 105 | Placebo N = 102
Vomiting | 11 | 6
Diarrhea | 6 | 7
Hematochezia | 4 | 0
Melena | 0 | 1
Anorexia | 0 | 4
Incision site lesion (drainage, oozing) | 11 | 6
Non-incision skin lesions (moist dermatitis, pyoderma) | 2 | 0
Otitis externa | 2 | 0
Positive joint culture | 1 | 0
Phlebitis | 1 | 0
Hematuria | 2 | 0
Conjunctivitis | 1 | 2
Splenomegaly | 1 | 0
Hepatomegaly | 1 | 0
Death | 0 | 1
^1 Dogs may have experienced more than one adverse reaction during the study.

This table does not include one dog that was dosed at 16.92 mg/kg/day for the study duration. Beginning on the last day of treatment, this dog experienced vomiting, diarrhea, increased water intake and decreased appetite. Hematology and clinical chemistry values were unremarkable. The dog recovered uneventfully within 3 days of cessation of dosing.

Incisional drainage was most prevalent in dogs enrolled at a single study site. There were no statistically significant changes in the mean values for hepatic or renal clinical pathology indices between DERAMAXX tablet- and placebo-treated dogs. Four DERAMAXX tablet-treated dogs and two placebo-treated dogs exhibited elevated bilirubin during the dosing phase. One DERAMAXX tablet-treated dog exhibited elevated ALT, BUN and total bilirubin and a single vomiting event. None of the changes in clinical pathology values were considered clinically significant.

The results of this clinical study demonstrate that DERAMAXX tablets, when administered daily for 7 days to control postoperative orthopedic pain and inflammation in dogs, are well tolerated.

Postoperative Dental Pain and Inflammation Field Study:

In this study, 62 dogs admitted to veterinary hospitals for dental extractions were randomly administered DERAMAXX tablets or a placebo. Drug administration started approximately 1 hour before surgery and continued once daily for 2 days postoperatively. Effectiveness was evaluated in 57 dogs and safety was evaluated in 62 dogs. There was a statistically significant reduction (p=0.0338) in the proportion of dogs that required rescue therapy to control post-surgical pain in the DERAMAXX treated group compared to the placebo control group. Pain assessors used a modification of the Glasgow Composite Pain Scale (mGCPS) to assess pain.^7 A dog was rescued if it scored ≥ 4 on the combined mGCPS variables of Posture/Activity, Demeanor, Response to Touch, and Vocalization, or if the investigator determined at any time that pain intervention was needed. The results of this field study demonstrate that DERAMAXX, when administered once daily for 3 days, is effective for the control of postoperative pain and inflammation associated with dental surgery.

Adverse Reactions:

A total of 62 male and female dogs of various breeds, 1.5-16 years old, were included in the field safety analysis. The following table shows the number of dogs displaying each adverse reaction. Digestive tract disorders (diarrhea and vomiting) and systemic disorders (abnormal clinical chemistry results) were the most frequently reported findings. There were no distinct breed, age, or sex predilections for adverse reactions that were reported. No dogs were withdrawn from the study due to the occurrence of an adverse reaction.

Abnormal Health Findings in the Dental Pain Field Study^1
Clinical Observation | DERAMAXX N = 31 | Placebo N = 31
Vomiting | 4 | 1
Diarrhea/soft stool | 3 | 1
Regurgitation | 0 | 2
Increased AST^2 | 3 | 0
Increased ALT^2 | 1 | 0
Hematuria | 1 | 0
Leukocytosis | 1 | 1
Neutrophilia | 1 | 1
Lameness | 1 | 0
Facial swelling | 0 | 1
Tachycardia | 0 | 1
^1 Dogs may have experienced more than one adverse reaction during the study.
^2 Included animals with results over 2x the high normal.

Post Approval Experience (Rev. 2010):

The following adverse events are based on post-approval adverse drug experience reporting. Not all adverse reactions are reported to FDA CVM. It is not always possible to reliably estimate the adverse event frequency or establish a causal relationship to product exposure using this data. The following adverse events are grouped by body system and are presented in decreasing order of reporting frequency.

Gastrointestinal: vomiting, diarrhea, hypoalbuminemia, melena, hematochezia, elevated amylase/lipase, hematemesis, abdominal pain, peritonitis, decreased or increased total protein and globulin, gastrointestinal perforation, gastrointestinal ulceration, hypersalivation.

General: anorexia, depression/lethargy, weight loss, weakness, fever, dehydration

Hepatic: elevated liver enzymes, hyperbilirubinemia, icterus, ascites, decreased BUN

Hematologic: anemia, leukocytosis, leukocytopenia, thrombocytopenia

Neurologic: seizures, ataxia, recumbency, trembling, confusion, collapse, hind limb paresis, nystagmus, proprioceptive disorder, vestibular signs

Behavioral: nervousness, hyperactivity, aggression, apprehension

Urologic: elevated BUN/creatinine, polydipsia, polyuria, hyper-phosphatemia, hematuria, low urine specific gravity, urinary incontinence, renal failure, urinary tract infection

Dermatologic: pruritus, erythema, urticaria, moist dermatitis, facial/muzzle edema, dermal ulceration/necrosis

Respiratory: panting, dyspnea, epistaxis, coughing

Cardiovascular: tachycardia, heart murmur, bradycardia, arrest

Sensory: Vestibular signs, glazed eyes, uveitis.

Ophthalmic: blindness, mydriasis, conjunctivitis, keratoconjunctivitis sicca, uveitis

In some cases, death has been reported as an outcome of the adverse events listed above.

To report suspected adverse drug events, contact Elanco Animal Health at 1-888-545-5973. For additional information about adverse drug experience reporting for animal drugs, contact FDA at 1-888-FDA-VETS or www.fda.gov/reportanimalae

For technical assistance, call Elanco Animal Health at 1-888-545-5973.

Chewable Tablets

Information for Dog Owners:

DERAMAXX, like other drugs of its class, is not free from adverse reactions. Owners should be advised of the potential for adverse reactions and be informed of the clinical signs associated with drug intolerance. Adverse reactions may include vomiting, diarrhea, decreased appetite, dark or tarry stools, increased water consumption, increased urination, anemia, yellowing of gums, skin or white of the eye due to jaundice, lethargy, incoordination, seizure, or behavioral changes. Serious adverse reactions associated with this drug class can occur without warning and in some cases result in death (see Warnings, Post-Approval Experience and Adverse Reactions). Owners should be advised to discontinue DERAMAXX therapy and contact their veterinarian immediately if signs of intolerance are observed.

The vast majority of patients with drug related adverse reactions have recovered when the signs are recognized, the drug is withdrawn, and veterinary care, if appropriate, is initiated. Owners should be advised of the importance of periodic follow up for all dogs during administration of any NSAID.

Storage Conditions:

DERAMAXX tablets should be stored at room temperature between 59° and 86°F (15-30°C).

Keep this and all medications out of reach of children.

How Supplied:

DERAMAXX tablets are available as 12 mg, 25 mg, 75 mg and 100 mg round, brownish, half-scored tablets in 7, 30, and 90 count bottles.

Manufactured for: Elanco US Inc.

Greenfield, IN 46140, USA

References:

1. Data on File
2. Data on File
3. Smith, et al.: “Pharmacological Analysis of Cyclo-oxygenase-1 in Inflammation,” Proc. Natl. Acad. Sci. USA (October 1998) 95: 13313-13318, Pharmacology.
4. Zhang, et al.: “Inhibition of Cyclo-oxygenase-2 Rapidly Reverses Inflammatory Hyperalgesia and Prostaglandin E2 Production,” JPET, (1997) 283: 1069-1075.
5. Verburg, KM et al. “Cox-2 Specific Inhibitors: Definition of a New Therapeutic Concept.” Amer J of Therapeutics 8, 49-64, 2001.
6. Data on File
7. Holton, L., Reid, J., Scott, E.M., Pawson, P. and Nolan, A. (2001). Development of a behaviour-based scale to measure acute pain in dogs. Veterinary Record, 148, 525-53.

Approve by FDA under NADA # 141-203

Revision date: February 2020

CA4980, CA4985,
CA4990, CA4995

PA102543X

Elanco™

INFORMATION FOR OWNERS/CAREGIVERS

Deramaxx™
(deracoxib)

Chewable Tablets

For Oral Use in Dogs Only

Do Not Use in Cats

Information for Dog Owners

DERAMAXX Chewable Tablets are for the control of pain and inflammation due to osteoarthritis or following orthopedic and dental surgery.

This summary contains important information about DERAMAXX tablets. You should read this information before starting your dog on DERAMAXX tablets. This sheet is provided only as a summary and does not take the place of instructions from your veterinarian. Talk to your veterinarian if you do not understand any of this information or you want to know more about DERAMAXX tablets.

What is DERAMAXX?

DERAMAXX tablets are a prescription non-steroidal anti-inflammatory drug (NSAID) of the coxib class. They are indicated for the control of postoperative pain and inflammation associated with orthopedic (bone) and dental surgery in dogs and for the control of pain and inflammation (soreness) associated with osteoarthritis in dogs. The tablets are flavored to make administration more convenient.

What kind of results can I expect when my dog takes DERAMAXX tablets for postoperative orthopedic and dental pain and inflammation?

DERAMAXX tablets allow your dog to recover more comfortably by controlling pain and inflammation that follow orthopedic and dental surgery.

- The postoperative orthopedic pain dose is a higher dose; administration at this dose should not exceed 7 days total, including the days the patient is administered DERAMAXX while in the hospital.
- Control of pain and inflammation may vary from dog to dog.
- If DERAMAXX tablets are not given according to your veterinarian's directions, your dog's pain may return.
- Consult your veterinarian if your dog appears to be uncomfortable.

What kind of results can I expect when my dog takes DERAMAXX tablets for pain and inflammation due to osteoarthritis?

Osteoarthritis is a painful condition caused by damage to cartilage and other parts of the joint that may result in the following changes or signs in your dog:

- Limping or lameness
- Decreased activity or exercise (reluctance to stand, climb stairs, jump or run, or difficulty in performing these activities)
- Stiffness or decreased movement of joints

While DERAMAXX is not a cure for osteoarthritis, it can control the pain and inflammation of osteoarthritis and improve your dog's mobility. Response may vary from dog to dog but can be quite dramatic. DERAMAXX tablets may need to be given on a periodic basis for the animal's lifetime. Use the lowest dose to provide adequate relief. Always consult with your veterinarian before altering the dose.

What dogs should not take DERAMAXX tablets?

Your dog should not be given DERAMAXX tablets if s/he:

- Has had an allergic reaction to deracoxib, the active ingredient in DERAMAXX tablets
- Has had an allergic reaction (such as hives, facial swelling, or red or itchy skin) to aspirin or other NSAIDs
- Is presently taking aspirin, other NSAIDs, or corticosteroids (unless directed by your veterinarian)
- Has bloody stool or vomit
- Has a pre-existing kidney or liver condition
- Has any condition predisposing to dehydration
- Is anorexic (loss of appetite)

DERAMAXX tablets should only be given to dogs. Do not use in cats.

People should not take DERAMAXX tablets. Keep DERAMAXX tablets and all medication out of reach of children. Call your physician immediately if you accidentally take DERAMAXX tablets.

What to discuss with your veterinarian before giving DERAMAXX tablets? Tell your veterinarian about:

- Any side effects your dog has experienced from DERAMAXX tablets or other NSAIDs
- Any digestive upset (vomiting or diarrhea) your dog has had
- Any kidney disease your dog has had
- Any other medical problems or allergies that your dog has now or has had in the past
- All medications that you are giving your dog or plan to give your dog, including those you can get without prescription and any dietary supplements
- If you plan to breed your dog, or if your dog is pregnant or nursing

Talk to your veterinarian about:

- The orthopedic or dental surgery your dog will undergo
- What tests might be done before surgery is performed or DERAMAXX tablets are prescribed
- The signs of pain or inflammation that may occur after surgery
- Normal events that can be expected after your dog undergoes surgery
- The proper amount of exercise after surgery to aid recovery
- The signs of osteoarthritis you have observed (for example, limping or stiffness)
- The importance of weight control, physical therapy and exercise in the management of osteoarthritis
- How often your dog may need to be examined by your veterinarian
- The risks and benefits of using DERAMAXX tablets

How to give DERAMAXX tablets to your dog.

DERAMAXX tablets should be given according to your veterinarian's instructions. Your veterinarian will tell you what amount of DERAMAXX tablets is right for your dog and for how long they should be given. Do not change the way you give DERAMAXX tablets to your dog without first speaking with your veterinarian. DERAMAXX tablets should be given by mouth and may be given with or without food, although with food is preferable.

What are the possible side effects that may occur in my dog during therapy with DERAMAXX tablets?

DERAMAXX tablets may cause some side effects in individual dogs. Serious side effects associated with this drug can occur with or without warning and, in some cases, result in death. The most common side effects associated with DERAMAXX therapy involve the digestive tract (vomiting, decreased appetite and diarrhea). Liver and kidney problems have also been reported. It is important to stop the medication and contact your veterinarian immediately if you think your dog may have a medical problem or side effect while on DERAMAXX tablets. If you have additional questions about possible side effects, talk with your veterinarian or call Elanco US Inc. at 1-888-545-5973.

Look for the following side effects that may indicate that your dog is having a problem with DERAMAXX tablets or may have another medical problem:

- Vomiting
- Decrease in appetite
- Change in behavior, such as depression, restlessness, aggression or apprehension
- Change in bowel movements such as diarrhea or change in stool color (black, tarry or bloody stool)
- Change in drinking or urination
- Yellowing of gums, skin or whites of the eyes (jaundice)

Can DERAMAXX tablets be given with other medications?

DERAMAXX tablets should not be given with other non-steroidal anti-inflammatory drugs (NSAIDs) or corticosteroids (for example, aspirin, carprofen, etodolac, prednisone).

Tell your veterinarian about all medications that you have given your dog in the past, and any medications that you are planning to give with DERAMAXX tablets. This should include any medications that you can get without a prescription and any dietary supplements. Your veterinarian may want to evaluate the potential for any drug interactions and to assure drug compatibility.

What can I do in case my dog eats more than the prescribed amount of DERAMAXX tablets?

Contact your veterinarian immediately if your dog eats more than the prescribed amount of DERAMAXX tablets.

What else should I know about DERAMAXX tablets?

This sheet provides a summary of information about DERAMAXX tablets. If you have any questions or concerns about DERAMAXX tablets, postoperative orthopedic and dental pain and inflammation, or osteoarthritis, talk to your veterinarian.

As with all prescribed medications, DERAMAXX tablets should only be given to the dog for which they are prescribed. They should be given to your dog only for the condition for which they were prescribed, at the prescribed dose, as directed by your veterinarian. It is important to periodically discuss your dog's response to DERAMAXX tablets at regular checkups. Your veterinarian will best determine if your dog is responding as expected and if your dog should continue receiving DERAMAXX tablets.

Approved by FDA under NADA # 141-203

Deramaxx, Elanco and the diagonal bar logo are trademarks of Elanco or its affiliates.

CA4980, CA4985 CA4990, CA4995

PA102543X

Elanco™

Principal Display Panel - Box Label

Deramaxx ™
(deracoxib)

12 mg
PER TABLET

Net contents:

7 chewable tablets

TRIAL PACK

For oral use
in dogs only.

Do not use
in cats.

Keep this
and all drugs
out of the reach
of children.

Principal Display Panel - Bottle Label

Deramaxx ™
(deracoxib)

12 mg Chewable Tablets

For Oral Use in Dogs Only

Do Not Use in Cats

A coxib-class NSAID

Caution: Federal law (U.S.) restricts this drug to
use by or on the order of a licensed veterinarian.

Approved by FDA under NADA # 141-203

Product of Switzerland. Manufactured for:

Elanco US Inc. Greenfield, IN 46140, USA

Elanco

7 tablets

Principal Display Panel - Bottle Label

Deramaxx ™
(deracoxib)

12 mg Chewable Tablets

For Oral Use in Dogs Only

Do Not Use in Cats

A coxib-class NSAID

Caution: Federal law (U.S.) restricts this drug to
use by or on the order of a licensed veterinarian.

Approved by FDA under NADA # 141-203

Product of Switzerland. Manufactured for:

Elanco US Inc. Greenfield, IN 46140, USA

Elanco

30 tablets

Principal Display Panel - Bottle Label

Deramaxx ™
(deracoxib)

12 mg Chewable Tablets

For Oral Use in Dogs Only

Do Not Use in Cats

A coxib-class NSAID

Caution: Federal law (U.S.) restricts this drug to
use by or on the order of a licensed veterinarian.

Approved by FDA under NADA # 141-203

Product of Switzerland. Manufactured for:

Elanco US Inc. Greenfield, IN 46140, USA

Elanco

90 tablets

Principal Display Panel - Box Label

Deramaxx ™
(deracoxib)

25 mg
PER TABLET

Net contents:

7 chewable tablets

TRIAL PACK

For oral use
in dogs only.

Do not use
in cats.

Keep this
and all drugs
out of the reach
of children.

Principal Display Panel - Bottle Label

Deramaxx ™
(deracoxib)

25 mg Chewable Tablets

For Oral Use in Dogs Only

Do Not Use in Cats

A coxib-class NSAID

Caution: Federal law (U.S.) restricts this drug to
use by or on the order of a licensed veterinarian.

Approved by FDA under NADA # 141-203

Product of Switzerland. Manufactured for:

Elanco US Inc. Greenfield, IN 46140, USA

Elanco

7 tablets

Principal Display Panel - Bottle Label

Deramaxx ™
(deracoxib)

25 mg Chewable Tablets

For Oral Use in Dogs Only

Do Not Use in Cats

A coxib-class NSAID

Caution: Federal law (U.S.) restricts this drug to
use by or on the order of a licensed veterinarian.

Approved by FDA under NADA # 141-203

Product of Switzerland. Manufactured for:

Elanco US Inc. Greenfield, IN 46140, USA

Elanco

30 tablets

Principal Display Panel - Bottle Label

Deramaxx ™
(deracoxib)

25 mg Chewable Tablets

For Oral Use in Dogs Only

Do Not Use in Cats

A coxib-class NSAID

Caution: Federal law (U.S.) restricts this drug to
use by or on the order of a licensed veterinarian.

Approved by FDA under NADA # 141-203

Product of Switzerland. Manufactured for:

Elanco US Inc. Greenfield, IN 46140, USA

Elanco

90 tablets

Principal Display Panel - Box Label

Deramaxx ™
(deracoxib)

75 mg
PER TABLET

Net contents:

7 chewable tablets

TRIAL PACK

For oral use
in dogs only.

Do not use
in cats.

Keep this
and all drugs
out of the reach
of children.

Principal Display Panel - Bottle Label

Deramaxx ™
(deracoxib)

75 mg Chewable Tablets

For Oral Use in Dogs Only

Do Not Use in Cats

A coxib-class NSAID

Caution: Federal law (U.S.) restricts this drug to
use by or on the order of a licensed veterinarian.

Approved by FDA under NADA # 141-203

Product of Switzerland. Manufactured for:

Elanco US Inc. Greenfield, IN 46140, USA

Elanco

7 tablets

Principal Display Panel - Bottle Label

Deramaxx ™
(deracoxib)

75 mg Chewable Tablets

For Oral Use in Dogs Only

Do Not Use in Cats

A coxib-class NSAID

Caution: Federal law (U.S.) restricts this drug to
use by or on the order of a licensed veterinarian.

Approved by FDA under NADA # 141-203

Product of Switzerland. Manufactured for:

Elanco US Inc. Greenfield, IN 46140, USA

Elanco

30 tablets

Principal Display Panel - Bottle Label

Deramaxx ™
(deracoxib)

75 mg Chewable Tablets

For Oral Use in Dogs Only

Do Not Use in Cats

A coxib-class NSAID

Caution: Federal law (U.S.) restricts this drug to
use by or on the order of a licensed veterinarian.

Approved by FDA under NADA # 141-203

Product of Switzerland. Manufactured for:

Elanco US Inc. Greenfield, IN 46140, USA

Elanco

90 tablets

Principal Display Panel - Box Label

Deramaxx ™
(deracoxib)

100 mg
PER TABLET

Net contents:

7 chewable tablets

TRIAL PACK

For oral use
in dogs only.

Do not use
in cats.

Keep this
and all drugs
out of the reach
of children.

Principal Display Panel - Bottle Label

Deramaxx ™
(deracoxib)

100 mg Chewable Tablets

For Oral Use in Dogs Only

Do Not Use in Cats

A coxib-class NSAID

Caution: Federal law (U.S.) restricts this drug to
use by or on the order of a licensed veterinarian.

Approved by FDA under NADA # 141-203

Product of Switzerland. Manufactured for:

Elanco US Inc. Greenfield, IN 46140, USA

Elanco

7 tablets

Principal Display Panel - Bottle Label

Deramaxx ™
(deracoxib)

100 mg Chewable Tablets

For Oral Use in Dogs Only

Do Not Use in Cats

A coxib-class NSAID

Caution: Federal law (U.S.) restricts this drug to
use by or on the order of a licensed veterinarian.

Approved by FDA under NADA # 141-203

Product of Switzerland. Manufactured for:

Elanco US Inc. Greenfield, IN 46140, USA

Elanco

30 tablets

Principal Display Panel - Bottle Label

Deramaxx ™
(deracoxib)

100 mg Chewable Tablets

For Oral Use in Dogs Only

Do Not Use in Cats

A coxib-class NSAID

Caution: Federal law (U.S.) restricts this drug to
use by or on the order of a licensed veterinarian.

Approved by FDA under NADA # 141-203

Product of Switzerland.

Manufactured for:

Elanco US Inc.

Greenfield, IN 46140, USA

Elanco

90 tablets